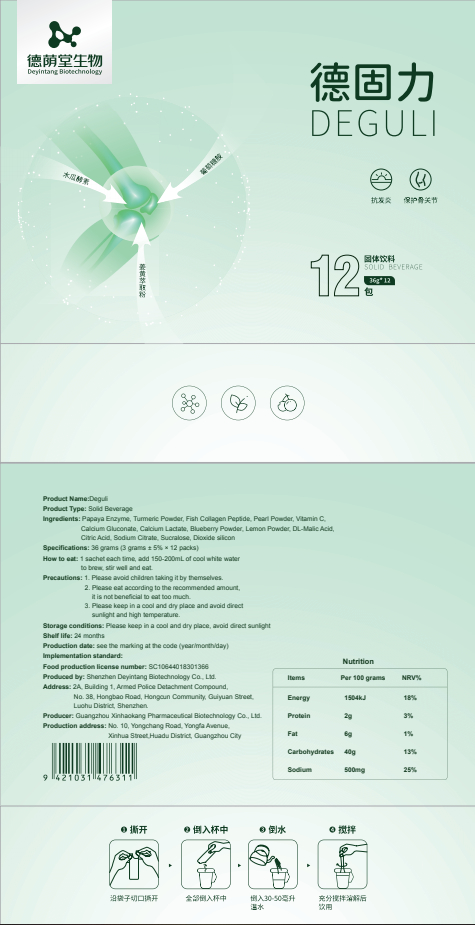 DRUG LABEL: Deguli
NDC: 82570-007 | Form: POWDER
Manufacturer: Shenzhen Deyintang Biotechnology Co., Ltd.
Category: otc | Type: HUMAN OTC DRUG LABEL
Date: 20220221

ACTIVE INGREDIENTS: PAPAIN 7 g/100 g; COLLAGEN, SOLUBLE, FISH SKIN 40 g/100 g; PEARL (HYRIOPSIS CUMINGII) 6 g/100 g; CURCUMA LONGA WHOLE 7 g/100 g; ASCORBIC ACID 4 g/100 g; GLUCAMINE 7 g/100 g
INACTIVE INGREDIENTS: CALCIUM GLUCONATE; BLUEBERRY; MALIC ACID; CITRIC ACID MONOHYDRATE; SODIUM CITRATE; CALCIUM LACTATE; SUCRALOSE; SILICON DIOXIDE

ACTIVE INGREDIENT

GLUCAMINE,Papaya Enzyme,Turmeric Powder, Fish Collagen Peptide, Pearl Powder,Vitamin C

INACTIVE INGREDIENT

Calcium Gluconate, Calcium Lactate, Blueberry Powder, Lemon Powder, DL-Malic Acid,Citric Acid,Sodium Citrate, Sucralose,Dioxide silicon

PURPOSE

health care

Please avoid children taking it by themselves.

DOSAGE AND ADMINISTRATION

1 sachet each time, add 150-200mL of cool white water to brew, stir well and eat.

INDICATIONS AND USAGE

Please eat according to the recommended amount,it is not beneficial to eat too much.

Storage conditions

Please keep in a cool and dry place, avoid direct sunlight

WARNINGS

1.Please avoid children taking it by themselves.
2.Please eat according to the recommended amount,it is not beneficial to eat too much.
3.Please keep in a cool and dry place and avoid direct sunlight and high temperature.